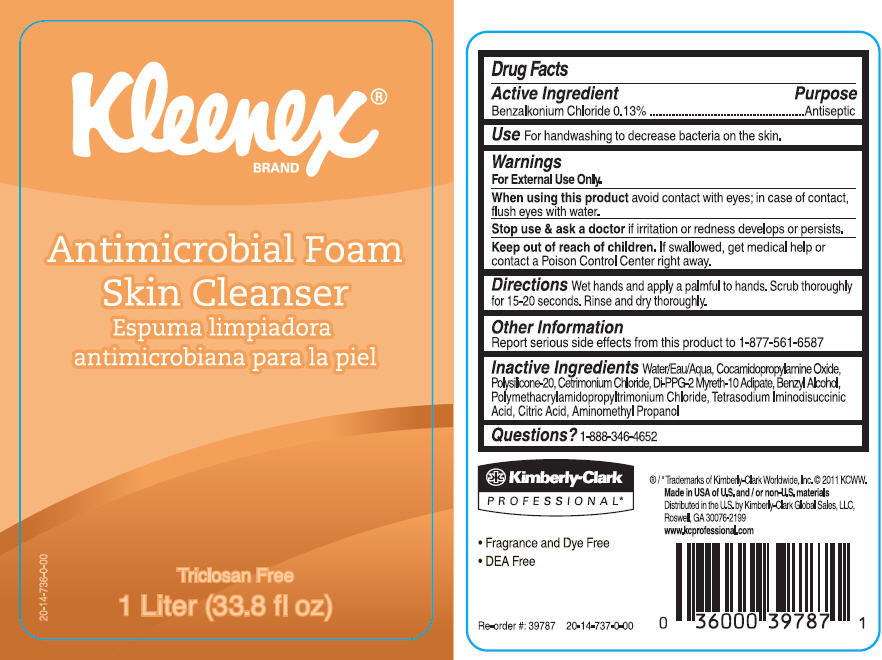 DRUG LABEL: KLEENEX Antimicrobial Skin Cleanser
NDC: 55118-440 | Form: SOLUTION
Manufacturer: Kimberly-Clark Corporation
Category: otc | Type: HUMAN OTC DRUG LABEL
Date: 20141112

ACTIVE INGREDIENTS: Benzalkonium Chloride 0.013 mg/1 L
INACTIVE INGREDIENTS: WATER; Cocamidopropylamine Oxide; Cetrimonium Chloride; Di-PPG-2 Myreth-10 Adipate; Benzyl Alcohol; Citric Acid Monohydrate; Aminomethylpropanol

KLEENEX® Antimicrobial Foam Skin Cleanser

Drug Facts

Active Ingredient

Benzalkonium Chloride 0.13%

Purpose

Antiseptic

Use

For handwashing to decrease bacteria on the skin.

Warnings

For External Use Only.

When using this product avoid contact with eyes; in case of contact, flush eyes with water.

Stop use & ask a doctor if irritation or redness develops or persists.

Keep out of reach of children. If swallowed, get medical help or contact a Poison Control Center right away.

Directions

Wet hands and apply a palmful to hands. Scrub thoroughly for 15-20 seconds. Rinse and dry thoroughly.

Other Information

Report serious side effects from this product to 1-877-561-6587

Inactive Ingredients

Water/Eau/Aqua, Cocamidopropylamine Oxide, Polysilicone-20, Cetrimonium Chloride, Di-PPG-2 Myreth-10 Adipate, Benzyl Alcohol, Polymethacrylamidopropyltrimonium Chloride, Tetrasodium Iminodisuccinic Acid, Citric Acid, Aminomethyl Propanol

Questions?

1-888-346-4652

Distributed in the U.S. by Kimberly-Clark Global Sales, LLC, Roswell, GA 30076-2199

PRINCIPAL DISPLAY PANEL - 1 Liter Bottle Label

Kleenex®
BRAND

Antimicrobial Foam
Skin Cleanser

Triclosan Free
1 Liter (33.8 fl oz)

20-14-736-0-00